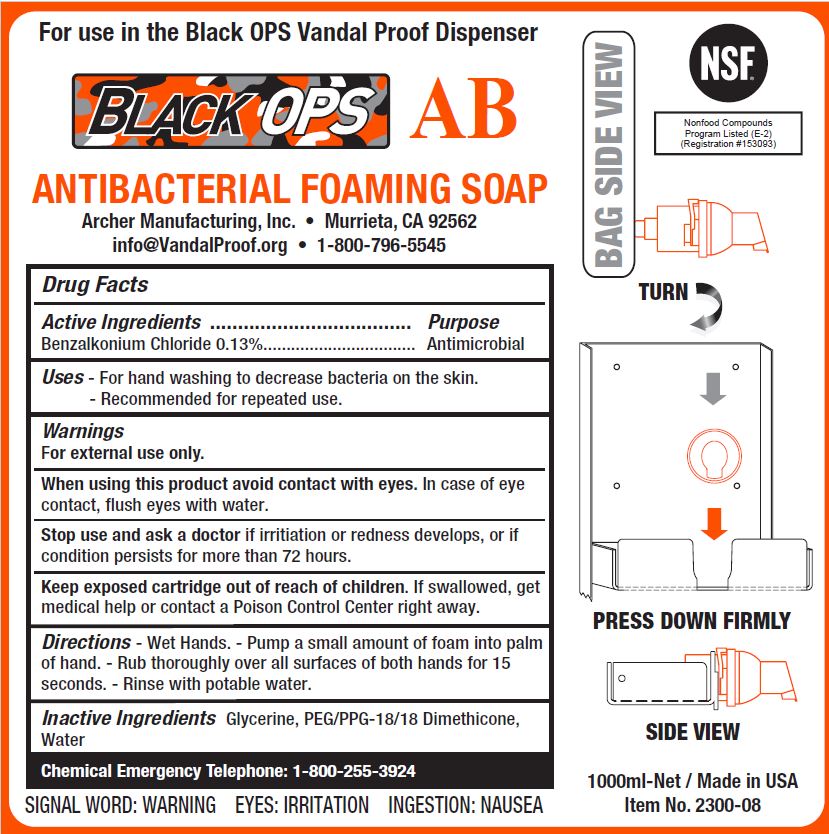 DRUG LABEL: BLACK OPS AB ANTIBACTERIAL FOAMING
NDC: 79016-103 | Form: SOAP
Manufacturer: Archer Manufacturing, Inc.
Category: otc | Type: HUMAN OTC DRUG LABEL
Date: 20241205

ACTIVE INGREDIENTS: BENZALKONIUM CHLORIDE 0.13 g/100 mL
INACTIVE INGREDIENTS: GLYCERIN; WATER; PEG/PPG-18/18 DIMETHICONE

ARCHER - BLACK OPS AB ANTIBACTERIAL FOAMING SOAP (79016-103)

ACTIVE INGREDIENTS

BENZALKONIUM CHLORIDE 0.13%

PURPOSE

ANTIMICROBIAL

USES

- FOR HAND WASHING TO HELP REDUCE BACTERIA ON THE SKIN.
- RECOMMENDED FOR REPEATED USE.

WARNINGS

FOR EXTERNAL USE ONLY.

WHEN USING THIS PRODUCT AVOID CONTACT WITH EYES. IN CASE OF EYE CONTACT, FLUSH WITH WATER.

STOP USE AND ASK A DOCTOR IF IRRITATION OR REDNESS DEVELOPS, OR IF CONDITION PERSISTS FOR MORE THAN 72 HOURS.

KEEP OUT OF REACH OF CHILDREN

KEEP EXPOSED CARTRIDGE OUT OF REACH OF CHILDREN. IF SWALLOWED, GET MEDICAL HELP OR CONTACT POISON CONTROL RIGHT AWAY.

DIRECTIONS

- Wet Hands. - Pump a small amount of foam into palm of hand.
- Rub thoroughly over all surfaces of both hands for 15 seconds.
- Rinse with potable water.

INACTIVE INGREDIENTS

Glycerine, PEG/PPG-18/18 Dimethicone, Water